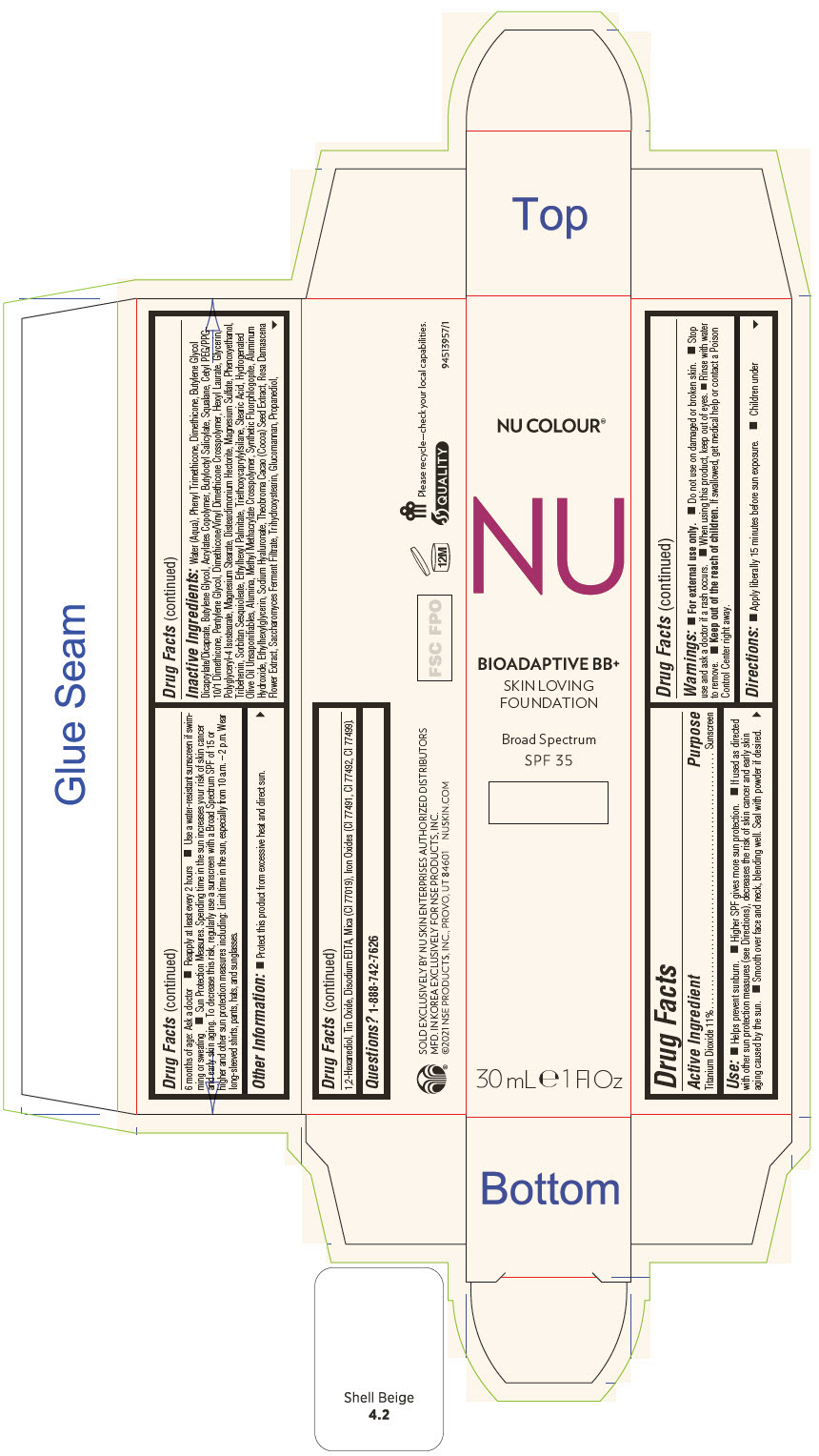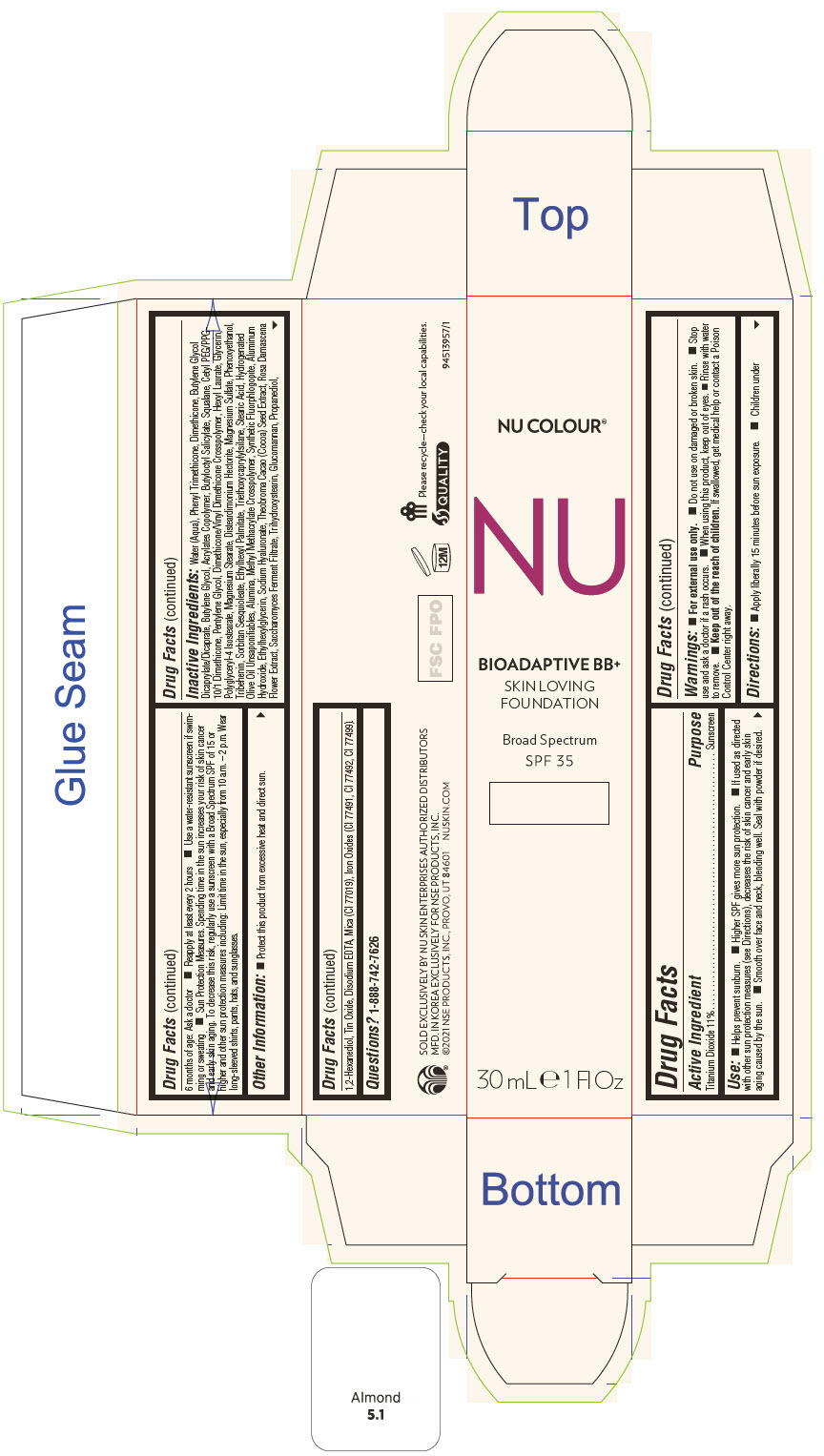 DRUG LABEL: Nu Colour Bioadaptive BB Plus Foundation - Shell Beige
NDC: 62839-3957 | Form: LOTION
Manufacturer: NSE Products, Inc.
Category: otc | Type: HUMAN OTC DRUG LABEL
Date: 20250103

ACTIVE INGREDIENTS: Titanium Dioxide 110 mg/1 mL
INACTIVE INGREDIENTS: Water; Phenyl Trimethicone; Dimethicone; BUTYLENE GLYCOL DICAPRYLATE/DICAPRATE; Butylene Glycol; FERRIC OXIDE YELLOW; BUTYLOCTYL SALICYLATE; Mica; Squalane; Pentylene Glycol; Hexyl Laurate; Glycerin; Polyglyceryl-4 Isostearate; Magnesium Stearate; Disteardimonium Hectorite; MAGNESIUM SULFATE, UNSPECIFIED FORM; Phenoxyethanol; FERRIC OXIDE RED; SORBITAN SESQUIOLEATE; TRIBEHENIN; Ethylhexyl Palmitate; Triethoxycaprylylsilane; Stearic Acid; FERROSOFERRIC OXIDE; Hydrogenated Olive Oil Unsaponifiables; ALUMINUM OXIDE; METHYL METHACRYLATE/GLYCOL DIMETHACRYLATE CROSSPOLYMER; MAGNESIUM POTASSIUM ALUMINOSILICATE FLUORIDE; ALUMINUM HYDROXIDE; Ethylhexylglycerin; ROSA X DAMASCENA FLOWERING TOP; EDETATE DISODIUM ANHYDROUS; COCOA; Trihydroxystearin; Propanediol; 1,2-Hexanediol; STANNIC OXIDE; HYALURONATE SODIUM; KONJAC MANNAN

Nu Colour® Bioadaptive BB+ Foundation

Drug Facts

Active Ingredient

Titanium Dioxide 11%

Purpose

Sunscreen

Use

- Helps prevent sunburn.
- Higher SPF gives more sun protection.
- If used as directed with other sun protection measures (see Directions), decreases the risk of skin cancer and early skin aging caused by the sun.
- Smooth over face and neck, blending well. Seal with powder if desired.

Warnings

- For external use only.

- Do not use on damaged or broken skin.

- Stop use and ask a doctor if a rash occurs.

- When using this product, keep out of eyes.
- Rinse with water to remove.

KEEP OUT OF REACH OF CHILDREN

- Keep out of the reach of children. If swallowed, get medical help or contact a Poison Control Center right away.

Directions

- Apply liberally 15 minutes before sun exposure.
- Children under 6 months of age: Ask a doctor
- Reapply at least every 2 hours
- Use a water-resistant sunscreen if swimming or sweating
- Sun Protection Measures. Spending time in the sun increases your risk of skin cancer and early skin aging. To decrease this risk, regularly use a sunscreen with a Broad Spectrum SPF of 15 or higher and other sun protection measures including: Limit time in the sun, especially from 10 a.m. – 2 p.m. Wear long-sleeved shirts, pants, hats, and sunglasses.

Other Information

- Protect this product from excessive heat and direct sun.

Inactive Ingredients

Water (Aqua), Phenyl Trimethicone, Dimethicone, Butylene Glycol Dicaprylate/Dicaprate, Butylene Glycol, Acrylates Copolymer, Butyloctyl Salicylate, Squalane, Cetyl PEG/PPG-10/1 Dimethicone, Pentylene Glycol, Dimethicone/Vinyl Dimethicone Crosspolymer, Hexyl Laurate, Glycerin, Polyglyceryl-4 Isostearate, Magnesium Stearate, Disteardimonium Hectorite, Magnesium Sulfate, Phenoxyethanol, Tribehenin, Sorbitan Sesquioleate, Ethylhexyl Palmitate, Triethoxycaprylylsilane, Stearic Acid, Hydrogenated Olive Oil Unsaponifiables, Alumina, Methyl Methacrylate Crosspolymer, Synthetic Fluorphlogopite, Aluminum Hydroxide, Ethylhexylglycerin, Sodium Hyaluronate, Theobroma Cacao (Cocoa) Seed Extract, Rosa Damascena Flower Extract, Saccharomyces Ferment Filtrate, Trihydroxystearin, Glucomannan, Propanediol, 1,2-Hexanediol, Tin Oxide, Disodium EDTA, Mica (CI 77019), Iron Oxides (CI 77491, CI 77492, CI 77499).

Questions?

1-888-742-7626

PRINCIPAL DISPLAY PANEL - 30 mL Tube Carton - Shell Beige

NU COLOUR®

NU

BIOADAPTIVE BB+
SKIN LOVING
FOUNDATION

Broad Spectrum
SPF 35

30 mL ℮ 1 Fl Oz

PRINCIPAL DISPLAY PANEL - 30 mL Tube Carton - Almond

NU COLOUR®

NU

BIOADAPTIVE BB+
SKIN LOVING
FOUNDATION

Broad Spectrum
SPF 35

30 mL ℮ 1 Fl Oz